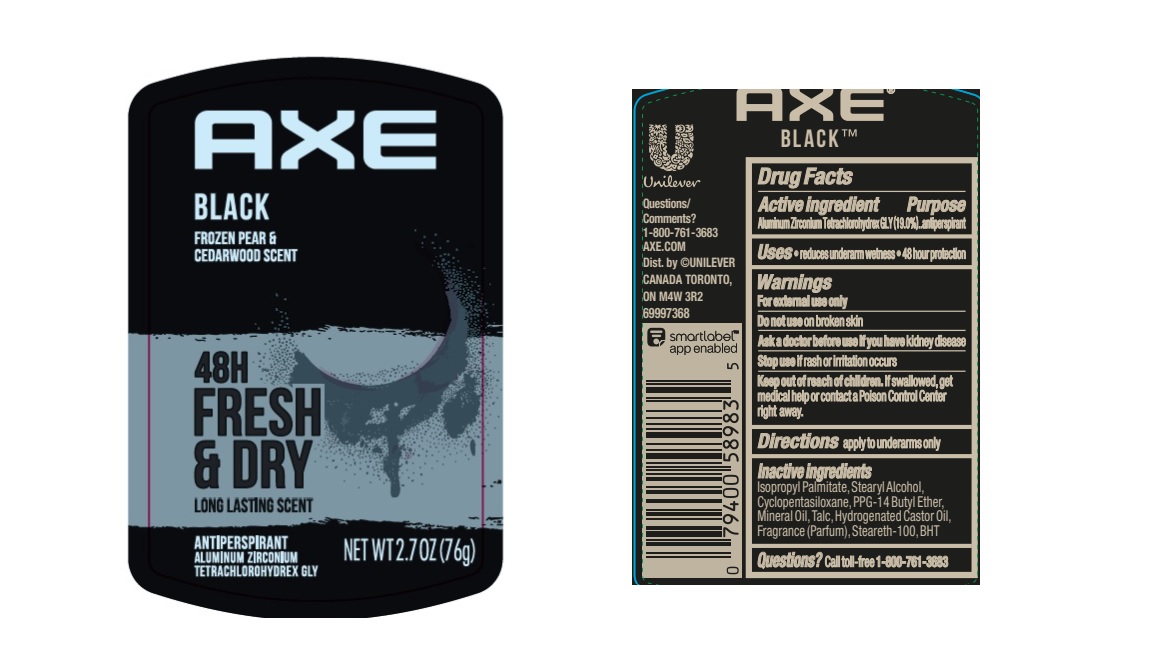 DRUG LABEL: Axe
NDC: 64942-2187 | Form: STICK
Manufacturer: Conopco Inc. d/b/a/ Unilever
Category: otc | Type: HUMAN OTC DRUG LABEL
Date: 20230906

ACTIVE INGREDIENTS: ALUMINUM ZIRCONIUM TETRACHLOROHYDREX GLY 19 g/100 g
INACTIVE INGREDIENTS: TALC; ISOPROPYL PALMITATE; CYCLOMETHICONE 5; HYDROGENATED CASTOR OIL; BUTYLATED HYDROXYTOLUENE; STEARYL ALCOHOL; PPG-14 BUTYL ETHER; MINERAL OIL; STEARETH-100; GERANIOL; LINALOOL, (+/-)-; COUMARIN; BENZYL BENZOATE; LIMONENE, (+)-; ISOMETHYL-.ALPHA.-IONONE; BENZYL SALICYLATE; .BETA.-CITRONELLOL, (R)-

AXE Black Frozen Pear & Cedarwood 48H Sweat & Odor Protection Antiperspirant

Drug Facts

Active ingredient

Aluminum Zirconium Tetrachlorohydrex GLY (19.0 %)

Purpose

antiperspirant

Uses

reduces underarm wetness

Warnings

• For externaluse only.
• Do not use on broken skin .
• Ask a doctor before use if you have kidney disease.
• Stop use if rash or irritation occurs.

• Keep out of reach of children.

If swallowed, get medical help or contact a Poison Control Center right away.

Directions

apply to underarms only

Inactive ingredients

Isopropyl Palmitate, Stearyl Alcohol, Cyclopentasiloxane, PPG-14 Butyl Ether, Mineral Oil, Talc, Hydrogenated Castor Oil, Fragrance (Parfum), Steareth-100, BHT, Alpha-Isomethyl Ionone, Benzyl Benzoate, Benzyl Salicylate, Citronellol, Coumarin, Geraniol, Limonene, Linalool

Questions?

Call toll-free 1-800-450-7580